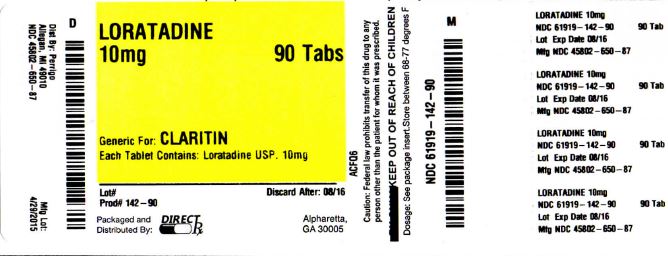 DRUG LABEL: LORATADINE
NDC: 61919-142 | Form: TABLET
Manufacturer: DIRECT RX
Category: otc | Type: HUMAN OTC DRUG LABEL
Date: 20151103

ACTIVE INGREDIENTS: LORATADINE 10 mg/1 1
INACTIVE INGREDIENTS: LACTOSE MONOHYDRATE; MAGNESIUM STEARATE; POVIDONE; STARCH, CORN

LORATADINE

USES

temporarily relieves these symptoms due to hay fever or other upper respiratory allergies:

- runny nosesneezing
- itchy, watery eyes
- itching of the nose or throat

ACTIVE INGREDIENT IN EACH TABLET

Loratadine 10 mg

PURPOSE

Antihistamine

WARNINGS

Do not use

if you have ever had an allergic reaction to this product or any of its ingredients

Ask a doctor before use if you have

liver or kidney disease. Your doctor should determine if you need a different dose.

When using this product

do not take more than directed. Taking more than directed may cause drowsiness.

Stop use and ask a doctor if

an allergic reaction to this product occurs. Seek medical help right away.

If pregnant or breast-feeding,

ask a health professional before use.

Keep out of reach of children.

In case of overdose, get medical help or contact a Poison Control Center right away.

DOSAGE AND ADMINISTRATION

adults and children 6 years and over

1 tablet daily; not more than 1 tablet in 24 hours

children under 6 years of age

ask a doctor

consumers with liver or kidney disease

ask a doctor

Other information

- do not use if printed foil under cap is broken or missing
- store at 20°-25°C (68°-77°F)

Questions or comments?

1-800-719-9260

INACTIVE INGREDIENTS

lactose monohydrate, magnesium stearate, povidone, pregelatinized starch

PRINCIPAL DISPLAY PANEL

Compare to Claritin® active ingredient

Loratadine Tablets, 10 mg

Antihistamine

24 Hour

Relief of:

Sneezing

Runny Nose

Itchy, Watery Eyes

Itchy Throat or Nose

Indoor & Outdoor Allergies

Non-Drowsy*

*When taken as directed. See Drug Facts Panel.

10mg Label Image: